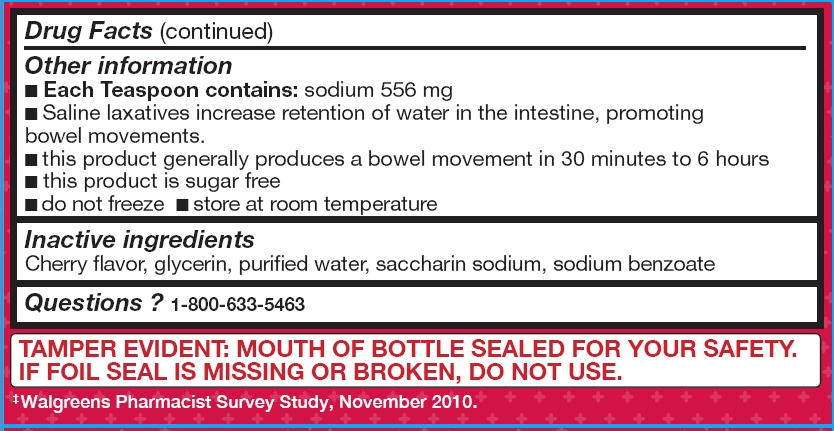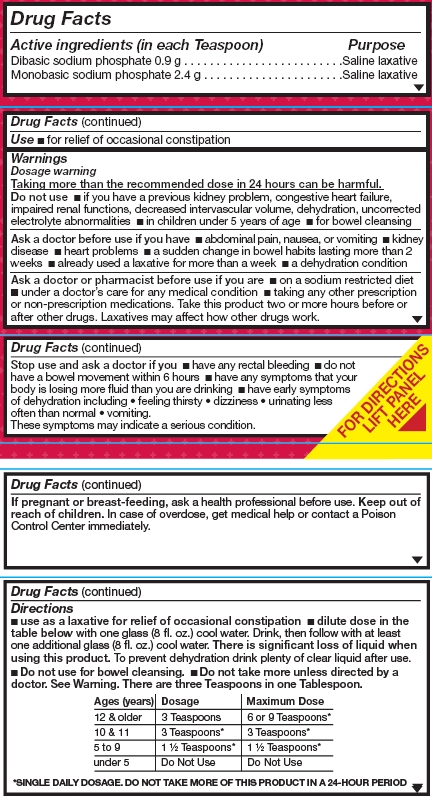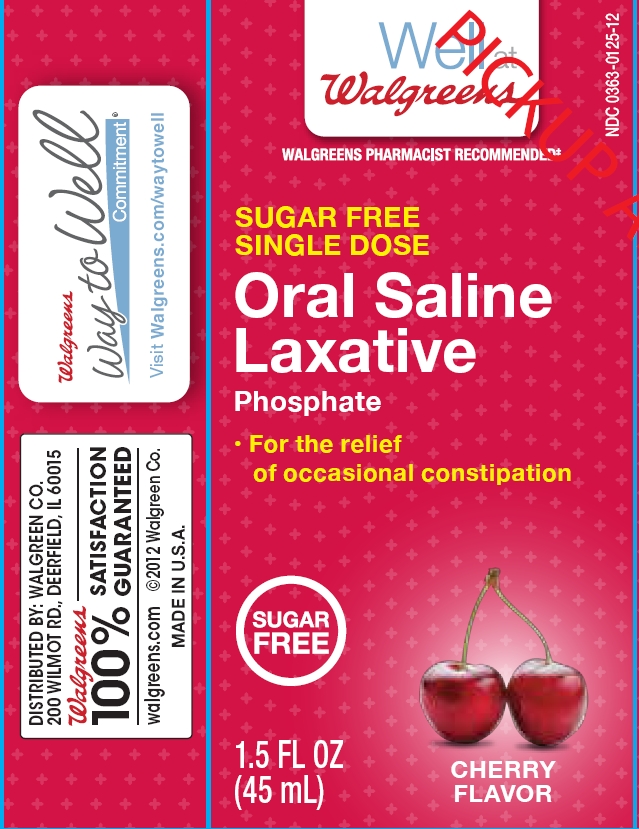 DRUG LABEL: Oral Saline Laxative
NDC: 0363-0126 | Form: LIQUID
Manufacturer: Walgreen Co
Category: otc | Type: HUMAN OTC DRUG LABEL
Date: 20131217

ACTIVE INGREDIENTS: SODIUM PHOSPHATE, DIBASIC .9 g/15 mL; SODIUM PHOSPHATE, MONOBASIC 2.4 g/15 mL
INACTIVE INGREDIENTS: GLYCERIN; WATER; SACCHARIN SODIUM; SODIUM BENZOATE

Drug Facts

Active ingredient (in each tablespoon)

Dibasic sodium phosphate .9 g

Monobasic sodium phosphate 2.4 g

Purpose

Saline laxative

Use

- for relief of occasional constipation

Warnings

Dosage warning

Taking more than the recommended dose in 24 hours can be harmful.

Do not use

- if you have a previous kidney problem, congestive heart failure, impaired renal functions, decreased intervascular volume, dehydration, uncorrected electrolyte abnormalities
- in children under 5 years of age
- for bowel cleansing

Ask a doctor before use if you have

- abdominal pain, nausea, or vomiting
- kidney disease
- heart problems
- a sudden change in bowel habits lasting more than 2 weeks
- already used a laxative for more than a week
- a dehydration condition

Ask a doctor or pharmacist before use if you are

- on a sodium restricted diet
- under a doctor’s care for any medical condition
- taking any other prescription or non-prescription medications. Take this product two or more hours before or after other drugs. Laxatives may affect how other drugs work.

Stop use and ask a doctor if you

- have any rectal bleeding
- do not have a bowel movement within 6 hours
- have any symptoms that your body is losing more fluid than you are drinking
- have early symptoms of dehydration including feeling thirsty, dizziness, urinating less often than normal, vomiting.
These symptoms may indicate a serious condition.

Keep out of reach of children.

In case of overdose, get medical help or contact a Poison Control Center immediately.

Directions

- use as a laxative for relief of occasional constipation
- dilute dose in the table below with one glass (8 fl. oz.) cool water. Drink, then follow with at least one additional glass (8 fl. oz.) cool water. There is significant loss of liquid when using this product. To prevent dehydration drink plenty of clear liquid after use.
- Do not use for bowel cleansing.
- Do not take more unless directed by a doctor. See Warning. There are three Teaspoons in one Tablespoon.

Ages (Years) | Dosage | Maximum Dose
12 & Older | 3 Teaspoons | 6 or 9 Teaspoons*
10 & 11 | 3 Teaspoons* | 3 Teaspoons*
5 to 9 | 1 1/2 Teaspoons* | 1 1/2 Teaspoons*
under 5 | Do Not Use | Do Not Use

*SINGLE DAILY DOSAGE. DO NOT TAKE MORE OF THIS PRODUCT IN A 24-HOUR PERIOD

Other information

- Each Teaspoon contains: sodium 556 mg
- Saline laxatives increase retention of water in the intestine, promoting bowel movements.
- this product generally produces a bowel movement in 30 minutes to 6 hours
- this product is sugar free
- do not freeze
- store at room temperature

TAMPER EVIDENT: Mouth of bottle sealed for your safety. If foil seal is missing or broken, do not use.

Inactive ingredients

Ginger Lime flavor, glycerin, purified water, saccharin sodium, sodium benzoate

Questions

1-800-633-5463

Package/Label Principal Display Panel

NDC 0363-0126-12

Well at Walgreens

SUGAR FREE

SINGLE DOSE

Oral Saline Laxative

Phosphate

- For relief of occasional constipation

Sugare Free

1.5 fl oz (45 mL)

GINGER LIME FLAVOR